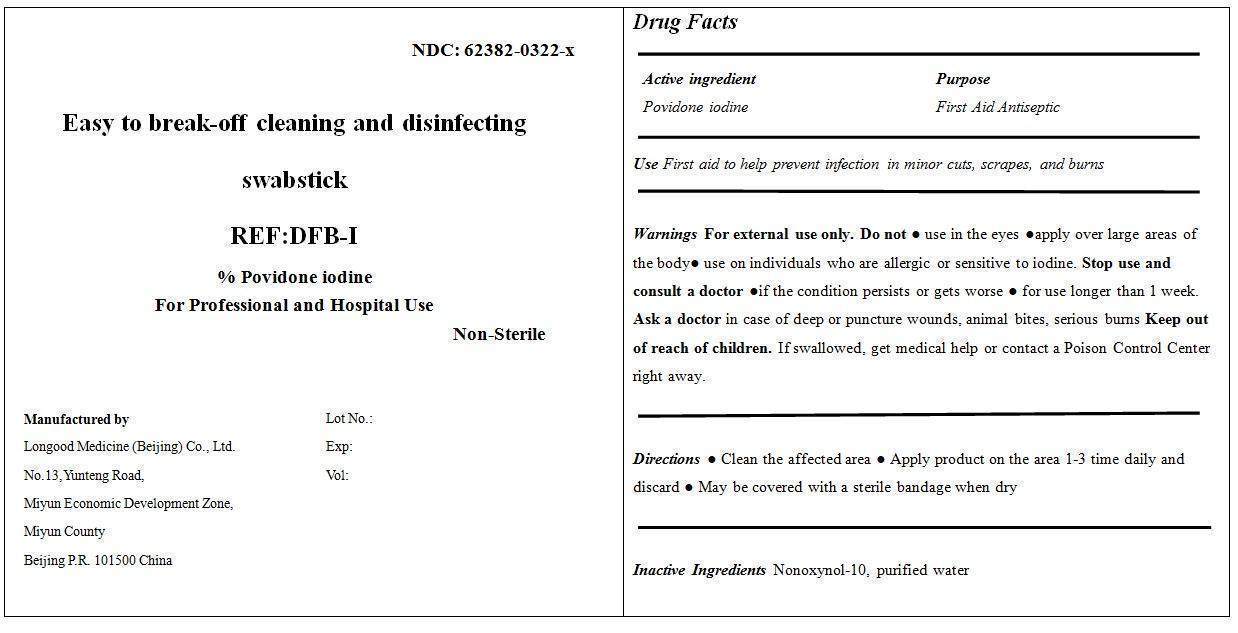 DRUG LABEL: Easy to break-off cleaning and disinfecting swabstick DFB-I
NDC: 62382-0322 | Form: SWAB
Manufacturer: Longood Medicine (Beijing) Co., Ltd.
Category: otc | Type: HUMAN OTC DRUG LABEL
Date: 20200106

ACTIVE INGREDIENTS: POVIDONE-IODINE 0.1 mg/1 mL
INACTIVE INGREDIENTS: WATER; NONOXYNOL-10

Drug Fact

Active Ingredient

Povidone Iodine 10%

Dosage

SWAB

Purpose

First Aid Antiseptic

Use

First aid to help prevent infection in minor cuts, scrapes, and burns

Warning

For external use only.

Do Not Use

● use in the eyes

●apply over large areas of the body

● use on individuals who are allergic or sensitive to iodine

Stop Use and Consult a Doctor

●if the condition persists or gets worse

● for use longer than 1 week. Ask a doctor in case of deep or puncture wounds, animal bites, serious burns

Keep out of reach of children

If swallowed, get medical help or contact a Poison Control Center right away.

Inactive Ingredient

Nonoxynol-10, Purified water